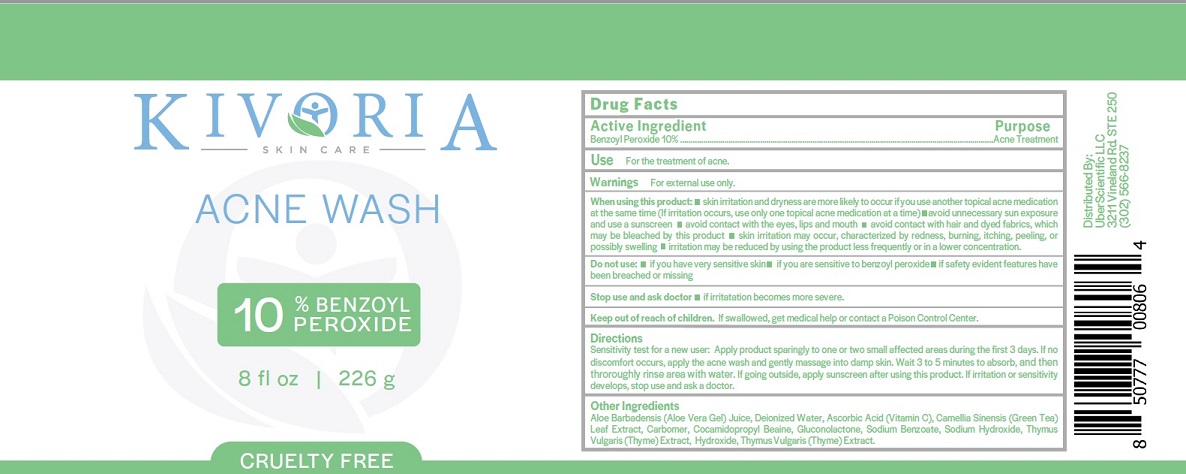 DRUG LABEL: Kivoria Acne Wash
NDC: 71131-100 | Form: SOAP
Manufacturer: UberScientific, LLC
Category: otc | Type: HUMAN OTC DRUG LABEL
Date: 20211228

ACTIVE INGREDIENTS: BENZOYL PEROXIDE 10 g/100 g
INACTIVE INGREDIENTS: ASCORBIC ACID; COCAMIDOPROPYL BETAINE; THYMUS VULGARIS LEAF; WATER; GREEN TEA LEAF; CARBOMER 934; GLUCONOLACTONE; HYDROXIDE ION; ALOE VERA LEAF; SODIUM BENZOATE; SODIUM HYDROXIDE

Kivoria Acne Wash (71131-100)

Drug Facts

Active Ingredient

Benzoyl Peroxide 10%

Purpose

Acne Treatment

Use

For the treatment of acne.

Warnings

For external use only.

When using this product

- Skin irritation and dryness are more likely to occur if you use another topical acne medication at the same time (if irritation occurs, use only one topcial acne medication at a time).
- Avoid unnecessary sun exposure and use a sunscreen
- Avoid contact with the eyes, lips, and mouth
- Avoid contact with hair and dyed fabrics, which may be bleached by this product
- Skin irritation may occur, characterized by redness, burning, itching, peeling, or possibly swelling
- Irritation may be reduced byusing the product less frequently or in a lower concentration.

Do Not Use

- If you have very sensitive skin
- If you are sensitive to benzoyl peroxide
- If safety evident features have been breached or missing

Stop use and ask a doctor

- If irritation becomes more severe

Keep out of reach of children.

If swallowed, get medical help or contact a Poison Control Center.

Directions

Sensitivity test for a new user: Apply product sparingly to one or two small affected areas during the first 3 days. If no discomfort occurs, apply the acne wash and gently massage into damp skin. Wait 3 to 5 minutes to absorb, and then thoroughly rinse area with water. If going outside, apply sunscreen after using this product. If irritation or sensitivity develops stop use and ask a doctor.

Other Ingredients

Aloe Barbadensis (aloe vera gel) Juice, Deionized Water, Ascorbic Acid (Vitamin C), Camella Sinensis (Green Tea) Leaf Extract, Carbomer, Cocamidopropyl Betaine, Gluconolactone, Sodium Benzoate, Sodium Hydroxide, Thymus Vulgaris (Thyme) Extract, Hydroxide, Thymus Vulgaris (Thyme) Extract.

Distributed by

Uber Scientific, LLC

3211 Vineland Rd. Suite 250

(302) 566-8237

PDP

KIVORIA Acne Wash

10% Benzoyl Peroxide

8fl oz | 226g

Cruelty Free

Made in USA